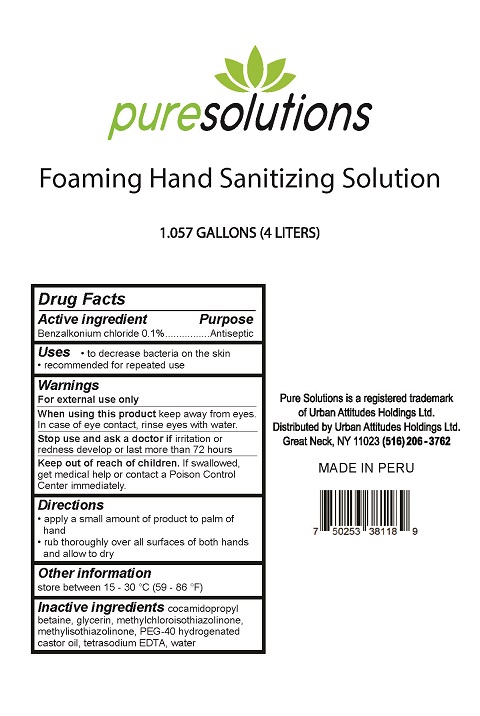 DRUG LABEL: Pure Solutions Foaming Hand Sanitizing
NDC: 77185-003 | Form: SOLUTION
Manufacturer: Urban Attitudes Holdings Ltd
Category: otc | Type: HUMAN OTC DRUG LABEL
Date: 20200607

ACTIVE INGREDIENTS: BENZALKONIUM CHLORIDE 0.1 g/0.1 L
INACTIVE INGREDIENTS: METHYLISOTHIAZOLINONE; POLYOXYL 40 HYDROGENATED CASTOR OIL; ETIDRONATE TETRASODIUM; METHYLCHLOROISOTHIAZOLINONE; COCAMIDOPROPYL BETAINE; WATER; GLYCERIN

Pure Solutions Foam Hand Sanitizer BZK

Drug Facts

Active ingredient

Benzalkonium chloride 0.1%

Purpose
Antiseptic

Uses

- to decrease bacteria on the skin
- recommended for repeated use

Warnings
For external use only.

When using this product keep away from eyes. In case of eye contact, rinse eyes with water.

Stop use and ask a doctor if irritation or redness develop or last more than 72 hours.

Keep out of reach of children. If swallowed, get medical help or contact a Poison Control Center immediately.

Directions

- apply a small amount of product to palm of hand
- rub thoroughly over all sufaces of both hands and allow to dry

Other information

store between 15-30°C (59-86°F)

Inactive ingredients

cocamidopropyl betaine, glycerin, methylchloroisothiazolinone, methylisothiazonlinone, PEG-40 hydrogenated castor oi, tetrasodium EDTA, water

Pure Solutions is a registered trademark of Urban Attitudes Holdings Ltd.

Distributed by: Urban Attititudes Holdings Ltd.

Great Neck, NY 11023 (516) 206-3672

MADE IN PERU

PACKAGE LABEL

puresolutions

Foaming Hand Sanitizing Solution

1.057 GALLONS (4 LITERS)